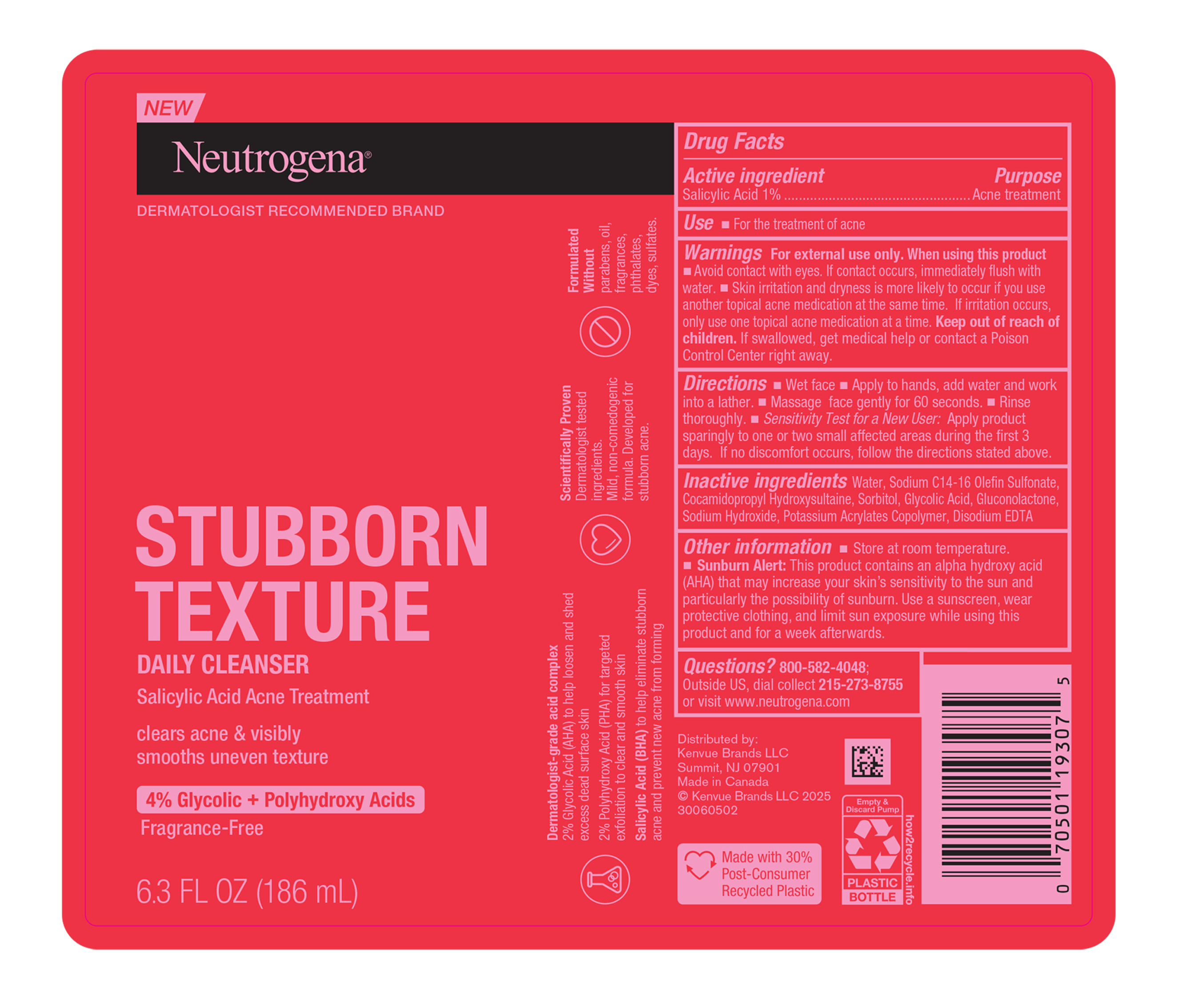 DRUG LABEL: Neutrogena Stubborn Texture Daily Cleanser
NDC: 69968-0704 | Form: GEL
Manufacturer: Kenvue Brands LLC
Category: otc | Type: HUMAN OTC DRUG LABEL
Date: 20250526

ACTIVE INGREDIENTS: SALICYLIC ACID 10 mg/1 mL
INACTIVE INGREDIENTS: WATER; SODIUM C14-16 OLEFIN SULFONATE; COCAMIDOPROPYL HYDROXYSULTAINE; SORBITOL; GLYCOLIC ACID; GLUCONOLACTONE; SODIUM HYDROXIDE; EDETATE DISODIUM

Neutrogena® STUBBORN TEXTURE DAILY CLEANSER

Drug Facts

Active ingredient

Salicylic Acid 1%

Purpose

Acne treatment

Use

- For the treatment of acne

Warnings

For external use only.

When using this product

- Avoid contact with eyes. If contact occurs, immediately flush with water.
- Skin irritation and dryness is more likely to occur if you use another topical acne medication at the same time. If irritation occurs, only use one topical acne medication at a time.

Keep out of reach of children. If swallowed, get medical help or contact a Poison Control Center right away.

Directions

- Wet face.
- Apply to hands, add water and work into a lather.
- Massage face gently for 60 seconds.
- Rinse thoroughly.
- Sensitivity Test for a New User: Apply product sparingly to one or two small affect areas during the first 3 days. If no discomfort occurs, follow the directions stated above.

Inactive ingredients

Water, Sodium C14-16 Olefin Sulfonate, Cocamidopropyl Hydroxysultaine, Sorbitol, Glycolic Acid, Gluconolactone, Sodium Hydroxide, Potassium Acrylates Copolymer, Disodium EDTA

Other information

- Store at room temperature.
- Sunburn Alert: This product contains an alpha hydroxy acid (AHA) that may increase your skin's sensitivity to the sun and particularly the possibility of sunburn. Use a sunscreen, wear protective clothing, and limit sun exposure while using this product and for a week afterwards.

Questions?

800-582-4048; Outside US, dial collect 215-273-8755 or visit www.neutrogena.com

Distributed by:

Kenvue Brands LLC
Summit, NJ 07901

PRINCIPAL DISPLAY PANEL - 186 mL Bottle Label

New
Neutrogena®
DERMATOLOGIST RECOMMENDED BRAND

STUBBORN
TEXTURE
DAILY CLEANSER
Salicylic Acid Acne Treatment

clears acne & visibly
smooths uneven texture

4% Glycolic + Polyhydroxy Acids
Fragrance-Free

6.3 FL OZ (186mL)